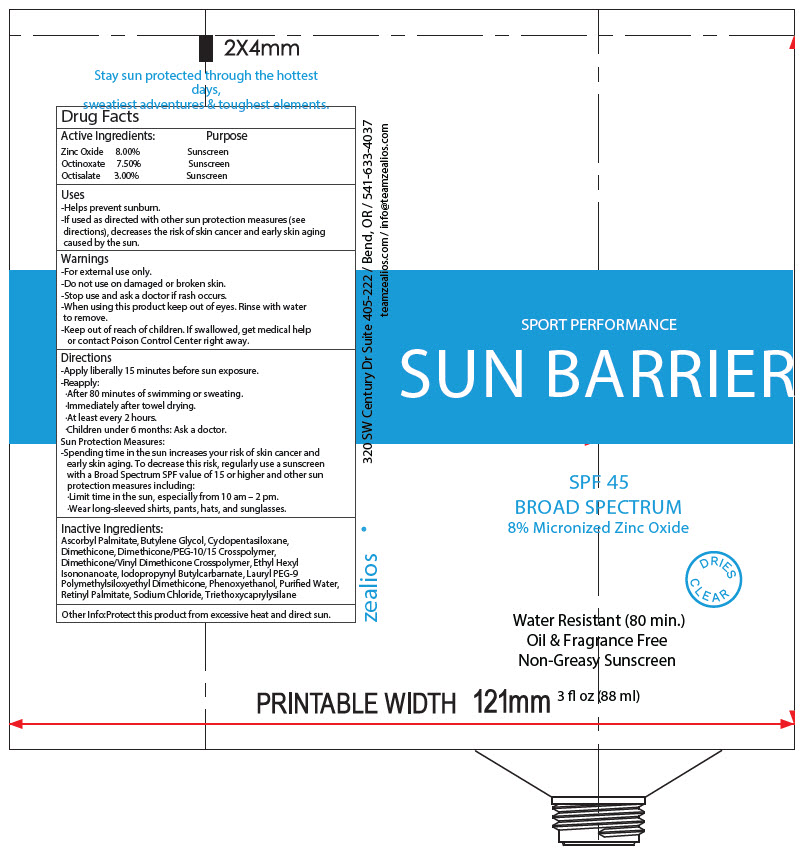 DRUG LABEL: Zealios Sun Barrier SPF 45
NDC: 83326-001 | Form: CREAM
Manufacturer: Personal Best Products Inc. dba Zealios
Category: otc | Type: HUMAN OTC DRUG LABEL
Date: 20231227

ACTIVE INGREDIENTS: ZINC OXIDE 80 mg/1 mL; OCTINOXATE 75 mg/1 mL; OCTISALATE 30 mg/1 mL
INACTIVE INGREDIENTS: ASCORBYL PALMITATE; BUTYLENE GLYCOL; CYCLOMETHICONE 5; DIMETHICONE; DIMETHICONE/PEG-10/15 CROSSPOLYMER; IODOPROPYNYL BUTYLCARBAMATE; LAURYL PEG-9 POLYDIMETHYLSILOXYETHYL DIMETHICONE; PHENOXYETHANOL; WATER; VITAMIN A PALMITATE; SODIUM CHLORIDE; TRIETHOXYCAPRYLYLSILANE

Zealios Sun Barrier SPF 45

Drug Facts

ACTIVE INGREDIENT

Active Ingredients: | Purpose
Zinc Oxide 8.00% | Sunscreen
Octinoxate 7.50% | Sunscreen
Octisalate 3.00% | Sunscreen

Uses

- Helps prevent sunburn.
- If used as directed with other sun protection measures (see directions), decreases the risk of skin cancer and early skin aging caused by the sun.

Warnings

- For external use only.
- Do not use on damaged or broken skin.
- Stop use and ask a doctor if rash occurs.
- When using this product keep out of eyes. Rinse with water to remove.

- Keep out of reach of children. If swallowed, get medical help or contact Poison Control Center right away.

Directions

- Apply liberally 15 minutes before sun exposure.
- Reapply:
  - After 80 minutes of swimming or sweating.
  - Immediately after towel drying.
  - At least every 2 hours.
  - Children under 6 months: Ask a doctor.

Sun Protection Measures:

- Spending time in the sun increases your risk of skin cancer and early skin aging. To decrease this risk, regularly use a sunscreen with a Broad Spectrum SPF value of 15 or higher and other sun protection measures including:
  - Limit time in the sun, especially from 10 am – 2 pm.
  - Wear long-sleeved shirts, pants, hats, and sunglasses.

Inactive Ingredients

Ascorbyl Palmitate, Butylene Glycol, Cyclopentasiloxane, Dimethicone, Dimethicone/PEG-10/15 Crosspolymer, Dimethicone/Vinyl Dimethicone Crosspolymer, Ethyl Hexyl Isononanoate, Iodopropynyl Butylcarbarnate, Lauryl PEG-9 Polymethylsiloxyethyl Dimethicone, Phenoxyethanol, Purified Water, Retinyl Palmitate, Sodium Chloride, Triethoxycaprylysilane

Other Info

Protect this product from excessive heat and direct sun.

PRINCIPAL DISPLAY PANEL - 88 ml Tube Label

SPORT PERFORMANCE
SUN BARRIER

SPF 45
BROAD SPECTRUM
8% Micronized Zinc Oxide

DRIES
CLEAR

Water Restant (80 min.)
Oil & Fragrance Free
Non-Greasy Sunscreen

3 fl oz (88 ml)